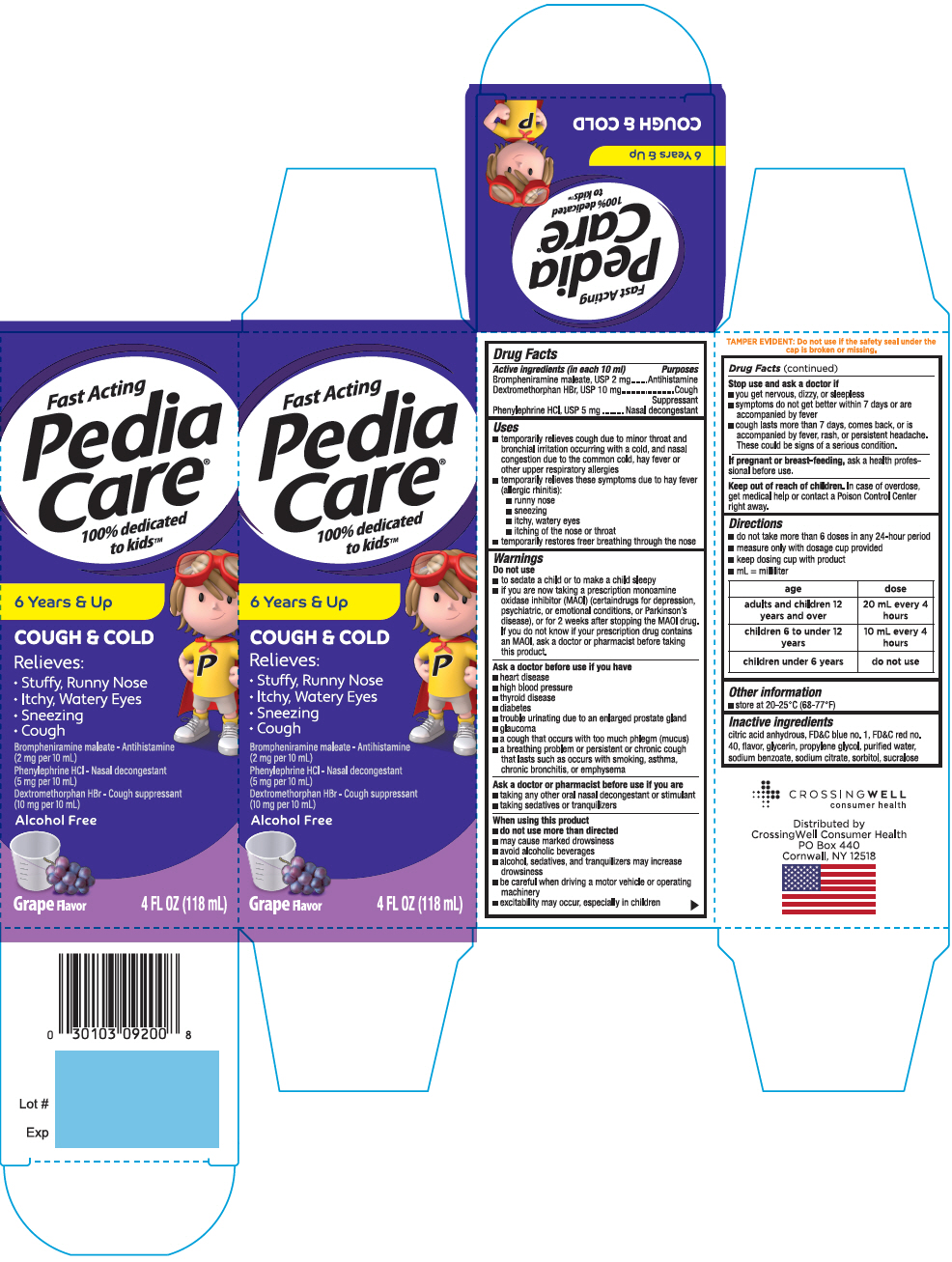 DRUG LABEL: Pediacare Childrens Cough and Cold Grape
NDC: 52412-920 | Form: SYRUP
Manufacturer: RANDOB LABS,LTD. DBA CROSSINGWELL CONSUMER HEALTH
Category: otc | Type: HUMAN OTC DRUG LABEL
Date: 20241230

ACTIVE INGREDIENTS: BROMPHENIRAMINE MALEATE 2 mg/10 mL; DEXTROMETHORPHAN HYDROBROMIDE 10 mg/10 mL; PHENYLEPHRINE HYDROCHLORIDE 5 mg/10 mL
INACTIVE INGREDIENTS: CITRIC ACID MONOHYDRATE; FD&C BLUE NO. 1; FD&C RED NO. 40; GLYCERIN; PROPYLENE GLYCOL; WATER; SODIUM BENZOATE; SODIUM CITRATE, UNSPECIFIED FORM; SORBITOL; SUCRALOSE

Pediacare®Children's Cough and Cold Grape

Drug Facts

ACTIVE INGREDIENT

PURPOSE

Active ingredients (in each 10 ml) | Purposes
Brompheniramine maleate, USP 2 mg | Antihistamine
Dextromethorphan HBr, USP 10 mg | Cough Suppressant
Phenylephrine HCl, USP 5 mg | Nasal decongestant

Uses

- temporarily relieves cough due to minor throat and bronchial irritation occurring with a cold, and nasal congestion due to the common cold, hay fever or other upper respiratory allergies
- temporarily relieves these symptoms due to hay fever (allergic rhinitis):
  - runny nose
  - sneezing
  - itchy, watery eyes
  - itching of the nose or throat
- temporarily restores freer breathing through the nose

Warnings

Do not use

- to sedate a child or to make a child sleepy
- if you are now taking a prescription monoamine oxidase inhibitor (MAOI) (certaindrugs for depression, psychiatric, or emotional conditions, or Parkinson's disease), or for 2 weeks after stopping the MAOI drug. If you do not know if your prescription drug contains an MAOI, ask a doctor or pharmacist before taking this product.

Ask a doctor before use if you have

- heart disease
- high blood pressure
- thyroid disease
- diabetes
- trouble urinating due to an enlarged prostate gland
- glaucoma
- a cough that occurs with too much phlegm (mucus)
- a breathing problem or persistent or chronic cough that lasts such as occurs with smoking, asthma, chronic bronchitis, or emphysema

Ask a doctor or pharmacist before use if you are

- taking any other oral nasal decongestant or stimulant
- taking sedatives or tranquilizers

When using this product

- do not use more than directed
- may cause marked drowsiness
- avoid alcoholic beverages
- alcohol, sedatives, and tranquilizers may increase drowsiness
- be careful when driving a motor vehicle or operating machinery
- excitability may occur, especially in children

Stop use and ask a doctor if

- you get nervous, dizzy, or sleepless
- symptoms do not get better within 7 days or are accompanied by fever
- cough lasts more than 7 days, comes back, or is accompanied by fever, rash, or persistent headache. These could be signs of a serious condition.

PREGNANCY OR BREAST FEEDING

If pregnant or breast-feeding,ask a health professional before use.

Keep out of reach of children.In case of overdose, get medical help or contact a Poison Control Center right away.

Directions

- do not take more than 6 doses in any 24-hour period
- measure only with dosage cup provided
- keep dosing cup with product
- mL = milliliter

age | dose
adults and children 12 years and over | 20 mL every 4 hours
children 6 to under 12 years | 10 mL every 4 hours
children under 6 years | do not use

Other information

- store at 20-25°C (68-77°F)

Inactive ingredients

citric acid anhydrous, FD&C blue no. 1, FD&C red no. 40, flavor, glycerin, propylene glycol, purified water, sodium benzoate, sodium citrate, sorbitol, sucralose

Distributed by
CrossingWell Consumer Health
PO Box 440
Cornwall, NY 12518

PRINCIPAL DISPLAY PANEL - 118 mL Bottle Carton

Fast Acting

Pedia
Care®

100% dedicated
to kids™

6 Years & Up

COUGH & COLD

Relieves:

- Stuffy, Runny Nose
- Itchy, Watery Eyes
- Sneezing
- Cough

Brompheniramine maleate - Antihistamine
(2 mg per 10 mL)

Phenylephrine HCl - Nasal decongestant
(5 mg per 10 mL)

Dextromethorphan HBr - Cough suppressant
(10 mg per 10 mL)

Alcohol Free

Grape Flavor

4 FL OZ (118 mL)